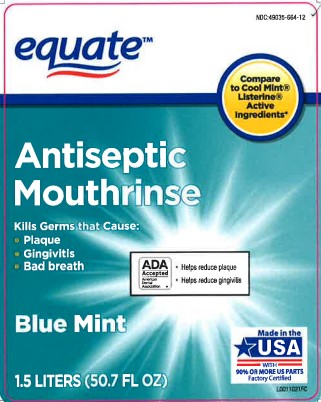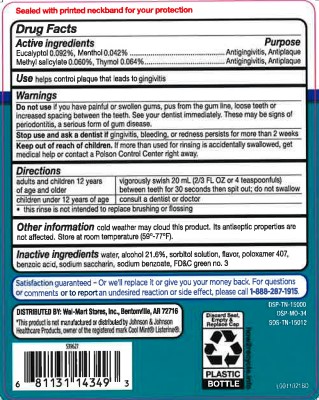 DRUG LABEL: Antispetic
NDC: 49035-664 | Form: MOUTHWASH
Manufacturer: Walmart Inc.
Category: otc | Type: HUMAN OTC DRUG LABEL
Date: 20260227

ACTIVE INGREDIENTS: EUCALYPTOL 0.92 mg/1 mL; MENTHOL 0.42 mg/1 mL; METHYL SALICYLATE 0.6 mg/1 mL; THYMOL 0.64 mg/1 mL
INACTIVE INGREDIENTS: WATER; ALCOHOL; SORBITOL; POLOXAMER 407; BENZOIC ACID; SACCHARIN SODIUM; SODIUM BENZOATE; FD&C GREEN NO. 3

Equate 664.003/664AT rev 2-664AU
Blue Mint Antiseptic Mouthrinse

Tamper Evident Statement

Sealed with printed neckband for your protection

Active ingredients

Eucalyptol 0.092%

Menthol 0.042%

Methyl salicylate 0.060%

Thymol 0.064%

Purpose

Antigingivitis, Antiplaque

Use

helps control plaque that leads to gingivitis

Warnings

for this product

Do not use

if you have painful or swollen gums, pus from the gum line, loose teeth or increased spacing between the teeth. See your dentist immediately. These may be signs of periodontitis, a serious form of gum disease.

Stop use and ask a dentist if

gingivitis, bleeding, or redness persists for more than 2 weeks.

Keep out of reach of children.

If more than used for rinsing is accidentally swallowed, get medical help or contact a Poison Control Center right away.

Directions

adults and children 12 years of age and older - vigorously swish 20 mL (2/3 FL OZ or 4 teaspoonfuls) between teeth for 30 seconds then spit out; do not swallow

children under 12 years of age - consult a dentist or doctor

- this rinse is not intended to replace brushing or flossing

Other information

cold weather may cloud this product. Its antiseptic properties are not affected. Store at room temperature (59° - 77°F).

Inactive ingredients

water, alcohol 21.6%, sorbitol solution, flavor, poloxamer 407, benzoic acid, sodium saccharin, sodium benzoate, FD&C green no.3

Adverse Reactions

Satisfaction guaranteed - Or we'll replace it or give you your money back. For questions or comments or to report and undesired reaction or side effect, please call 1-888-287-1915.

DISTRIBUTED BY: Wal-Mart Stores, Inc., Bentonville, AR 72716

*This product is not manufactured or distributed by Johnson & Johnson Healthcare Products, owner of the registered mark Cool Mint®Listerine®.

Discar Seal, Empty & Replace Cap

PLASTIC BOTTLE

how2recycle.info

DSP-TN-15000

DSP-MO-34

SDS-TN-15012

principal display panel

equate™

NDC: 49035-664-12

Compare to Cool Mint® Listerine® Active Ingredients*

Antiseptic

Mouthrinse

Kills Germs that Cause:

- Plaque
- Gingivitis
- Bad Breath

ADA Accepted

American Dental Association

- Helps reduce plaque
- Helps reduce gingivitis

Blue Mint

Made in USA with 90% or more US parts

Factory Certified

1.5 Liters (50.7 FL OZ)